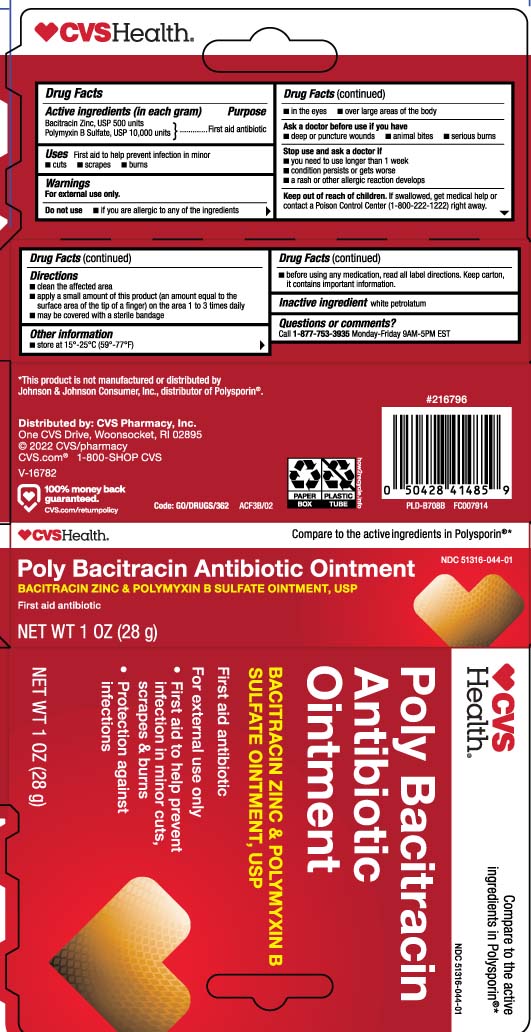 DRUG LABEL: Antibiotic
NDC: 51316-044 | Form: OINTMENT
Manufacturer: CVS PHARMACY, INC
Category: otc | Type: HUMAN OTC DRUG LABEL
Date: 20240315

ACTIVE INGREDIENTS: BACITRACIN ZINC 500 [iU]/1 g; POLYMYXIN B SULFATE 10000 [iU]/1 g
INACTIVE INGREDIENTS: PETROLATUM

Antibiotic Ointment (Bacitracin Zinc, Neomycin Sulfate, Polymyxin B Sulfate)

Active ingredients (in each gram)

Bacitracin zinc, USP 500 units
Polymyxin B sulfate, USP 10,000 units

Purpose

First aid antibiotic

Uses

First aid to help prevent infection in

- cuts
- scrapes
- burns

Warnings

For external use only

Do not use

- if you are allergic to any of the ingredients
- in the eyes
- over large areas of the body

Ask a doctor before use if you have

- deep or puncture wounds
- animal bites
- serious burns

Stop use and ask a doctor if

- you need to use longer than 1 week
- condition persists or gets worse
- a rash or other allergic reaction develops

Keep out of reach of children.

If swallowed, get medical help or contact a Poison Control Center (1-800-222-1222) right away.

Directions

- clean affected area
- apply a small amount of this product (an amount equal to the surface area of the tip of a finger) on the area 1 to 3 times daily
- may be covered with a sterile bandage

Other information

- Store at 15º-25ºC (59º-77ºF)
- Before using any medication, read all label directions. Keep carton, it contains important information.

Inactive ingredient

white petrolatum

Questions or comments?

Call 1-877-753-3935 Monday-Friday 9AM-5PM EST

Principal display panel

Compare to the active ingredients in Polysporin®*

Poly Bacitracin Antibiotic Ointment

BACITRACIN ZINC & POLYMYXIN B SULFATE OINTMENT, USP

First aid antibiotic

For External Use Only

- First Aid to Help Prevent Infection in Minor Cuts, Scrapes, and Burns
- Protection Against Infection

*This product is not manufactured or distributed by Johnson & Johnson Consumer, Inc., distributor of Polysporin®.

Distributed by: CVS Pharmacy, Inc.

One CVS Drive, Woonsocket, RI 02895

Package label

CVS HEALTH Antibiotic Ointment